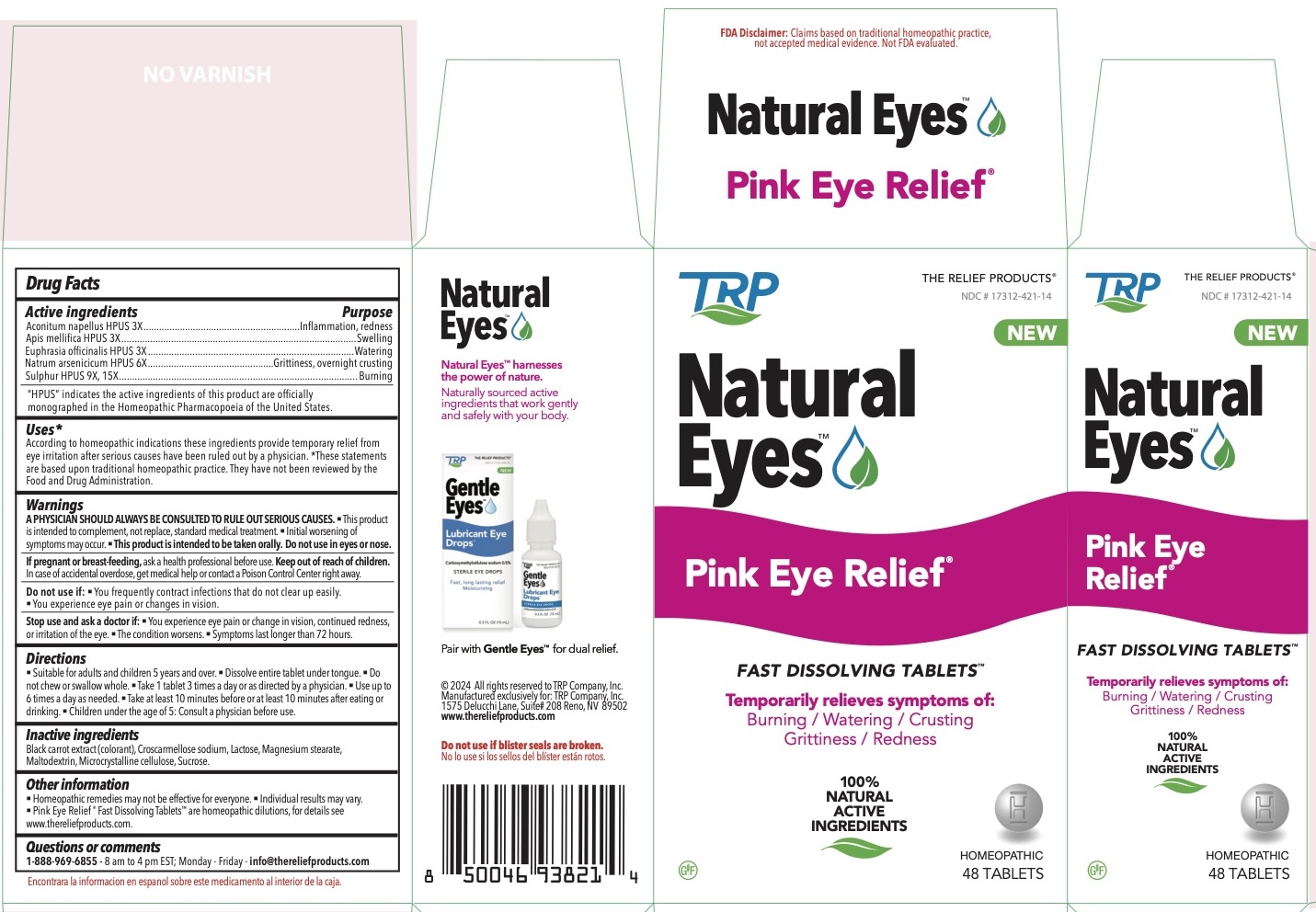 DRUG LABEL: Natural Eyes Pink Eye Relief
NDC: 17312-463 | Form: TABLET, ORALLY DISINTEGRATING
Manufacturer: TRP Company
Category: homeopathic | Type: HUMAN OTC DRUG LABEL
Date: 20250319

ACTIVE INGREDIENTS: ACONITUM NAPELLUS 3 [hp_X]/1 1; SULFUR 9 [hp_X]/1 1; SODIUM ARSENATE, DIBASIC, HEPTAHYDRATE 6 [hp_X]/1 1; EUPHRASIA STRICTA 3 [hp_X]/1 1; APIS MELLIFERA 3 [hp_X]/1 1
INACTIVE INGREDIENTS: CROSCARMELLOSE SODIUM; BLACK CARROT; LACTOSE; CELLULOSE, MICROCRYSTALLINE; MALTODEXTRIN; MAGNESIUM STEARATE; SUCROSE

Natural Eyes Pink Eye Relief 70 Fast Dissolving Tables

ACTIVE INGREDIENT

Aconitum napellus 3X...

Apis mellifica 3X

Euphrasia officinalis 3X

Natrum arsenicicum 6X

Sulphur 9X, 15X

PURPOSE

Aconitum napellus - Inflammation, redness

Apis mellifica - Swelling

Euphrasia officinalis - Watering

Natrum arsenicicum - Grittiness, overnight crusting

Sulphur - Burning

Uses*
According to homeopathic indications these ingredients provide temporary relief from eye irritation after serious causes have been ruled out by a physician.
*These statements are based upon traditional homeopathic practice. They have not been reviewed by the Food and Drug Administration.

Warnings:
A PHYSICIAN SHOULD ALWAYS BE CONSULTED TO RULE OUT SERIOUS CAUSES.

- This product is intended to complement, not replace, standard medical treatment.
- Initial worsening of symptoms may occur.

- This product is intended to be taken orally. Do not use in eyes or nose.

PREGNANCY OR BREAST FEEDING

If pregnant or breast-feeding, ask a health professional before use.

Keep out of reach of children.

WARNINGS

- In case of overdose, get medical help or contact a Poison Control Center right away.

Stop use and ask a doctor if:

• You experience eye pain or change in vision, continued redness, or irritation of the eye. • The condition worsens.
• Symptoms last longer than 72 hours.

Directions

- Suitable for adults and children ages 5 and over.
- Dissolve entire tablet under tongue.
- Do not chew or swallow whole.
- Take 1 tablet 3 times a day or as directed by a physician.
- Use up to 6 times a day as needed.
- Take at least 10 minutes before or at least 10 minutes after eating or drinking.
- Children under the age of 5: Consult a physician before use.

Other information

- Homeopathic remedies may not be effective for everyone.
- Individual results may vary.
- Pink Eye Relief ® Fast Dissolving TabletsTM are homeopathic dilutions, for details see www.thereliefproducts.com

Inactive ingredients

Black carrot extract (colorant), Croscarmellose sodium, Lactose, Magnesium stearate, Maltodextrin, Microcrystalline cellulose, Sucrose.

Do not use if:

• You frequently contract infections that do not clear up easily. • You experience eye pain or changes in vision.

Questions or comments? 888-969-6855

8 am to 4 pm EST; Monday - Friday
www.thereliefproducts.com